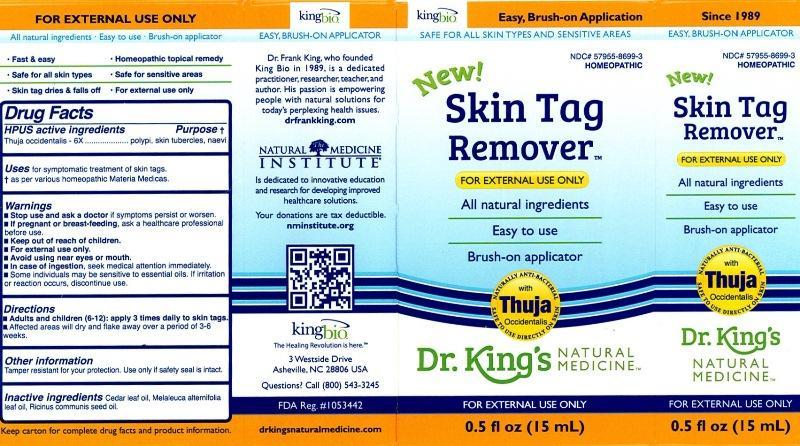 DRUG LABEL: Skin Tag Remover
NDC: 57955-8699 | Form: LIQUID
Manufacturer: King Bio Inc.
Category: homeopathic | Type: HUMAN OTC DRUG LABEL
Date: 20140108

ACTIVE INGREDIENTS: THUJA OCCIDENTALIS LEAFY TWIG 6 [hp_X]/15 mL
INACTIVE INGREDIENTS: CEDAR LEAF OIL; TEA TREE OIL; CASTOR OIL

Skin Tag Remover

ACTIVE INGREDIENT

Drug Facts_______________________________________________________________________________

HPUS active ingredients

Thuja occidentalis 6X

INDICATIONS AND USAGE

Uses for symptomatic treatment of skin tags.

† as per various homeopathic Materia Medicas.

Warnings

- Stop use and ask a doctor if symptoms persist or worsen.
- If pregnant or breast-feeding, ask a healthcare professional before use.
- Keep out of reach of children.
- For external use only.
- Avoid using near eyes or mouth.
- In case if ingestion, seek medical attention immediately.
- Some individuals may be sensitive to essential oils. If irritation or reaction occurs, discontinue use.

- Keep out of reach of children.

Directions

- Adults and children (6-12): apply 3 times daily to skin tags.
- Affected areas will dry and flake away over a period of 3-6 weeks.

Other Information

Tamper resistant for your protection. Use only if safety seal is intact.

Inactive Ingredients

Cedar leaf oil, Melaleuca alternifolia leaf oil, Ricinus communis seed oil.

PURPOSE

Drug Facts________________________________________________________________________________

HPUS active ingredients Purpose†

Thuja occidentalis - 6X..................................................polypi, skin tubercles, naevi